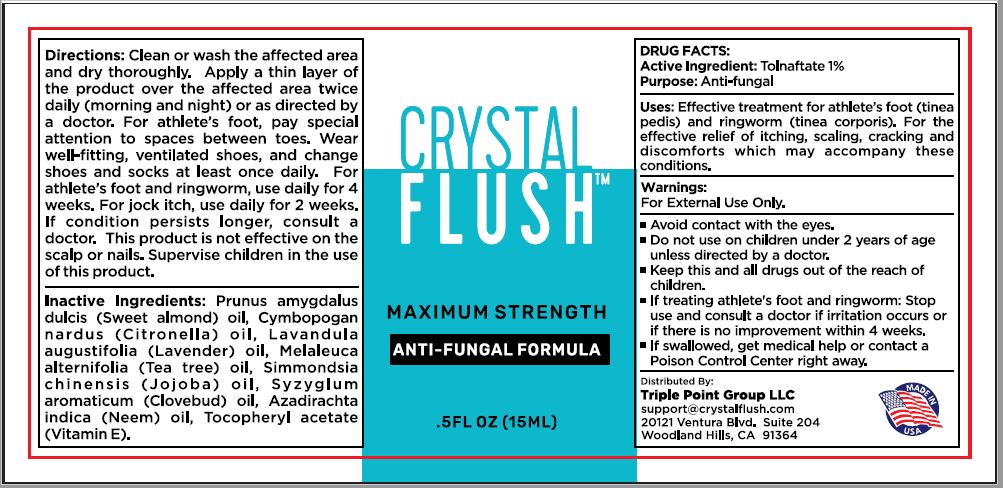 DRUG LABEL: CRYSTAL FLUSH
NDC: 80569-101 | Form: SOLUTION
Manufacturer: Triple Point Group, LLC
Category: otc | Type: HUMAN OTC DRUG LABEL
Date: 20210428

ACTIVE INGREDIENTS: TOLNAFTATE 1 g/100 mL
INACTIVE INGREDIENTS: ALMOND OIL; CITRONELLA OIL; LAVENDER OIL; TEA TREE OIL; JOJOBA OIL; CLOVE OIL; AZADIRACHTA INDICA SEED OIL; .ALPHA.-TOCOPHEROL ACETATE

CRYSTAL FLUSH Maximum Strength Anti-Fungal Formula

Active Ingredient

Tolnaftate 1%

Purpose:

Anti-fungal

Uses:

Effective treatment for athlete's foot (tinea pedis) and ringworm (tinea corporis). For the effective relief of itching, scaling, cracking and discomforts which may accompany these conditions.

Warnings:

For external use only.

- Avoid contact with the eyes.
- Do not use on children under 2 years of age unless directed by a doctor.

- If treating athlete's foot and ringworms: Stop use and consult a doctor if irritation occurs or if there is no improvement within 4 weeks.
- If swallowed, get medical help or contact a Poison Control Center right away.

KEEP OUT OF REACH OF CHILDREN

Keep this and all drugs out of the reach of children.

Directions:

Clean or wash the affected area and dry throughly. Apply a thin layer of the product over the affected area twice daily (morning and night) or as directed by doctor. For athletes foot, pay special attention to space between toes. Wear well-fitting, ventilated shoes, and change shoes and socks at least once daily. For athlete's foot and ringworm, use daily for 4 weeks. For jock itch, use daily for 2 weeks. If condition persists longer, consult a doctor. This product is not effective on the scalp or nails. Supervise children in the use of this product.

Inactive ingredients:

Prunus Amygdalus Dulcis (Sweet Almond) Oil, Cymbopogan Nardus (Citronella) Oil, Lavandula Angustifolia (Lavender) Oil, Melaleuca Alternifolia (Tea Tree) Oil, Simmondsia Chinensis (Jojoba) Oil, Syzygium Aromaticum (Clovebud) Oil, Azadirachta Indica (Neem) oil, Tocopheryl Acetate (Vitamin E).